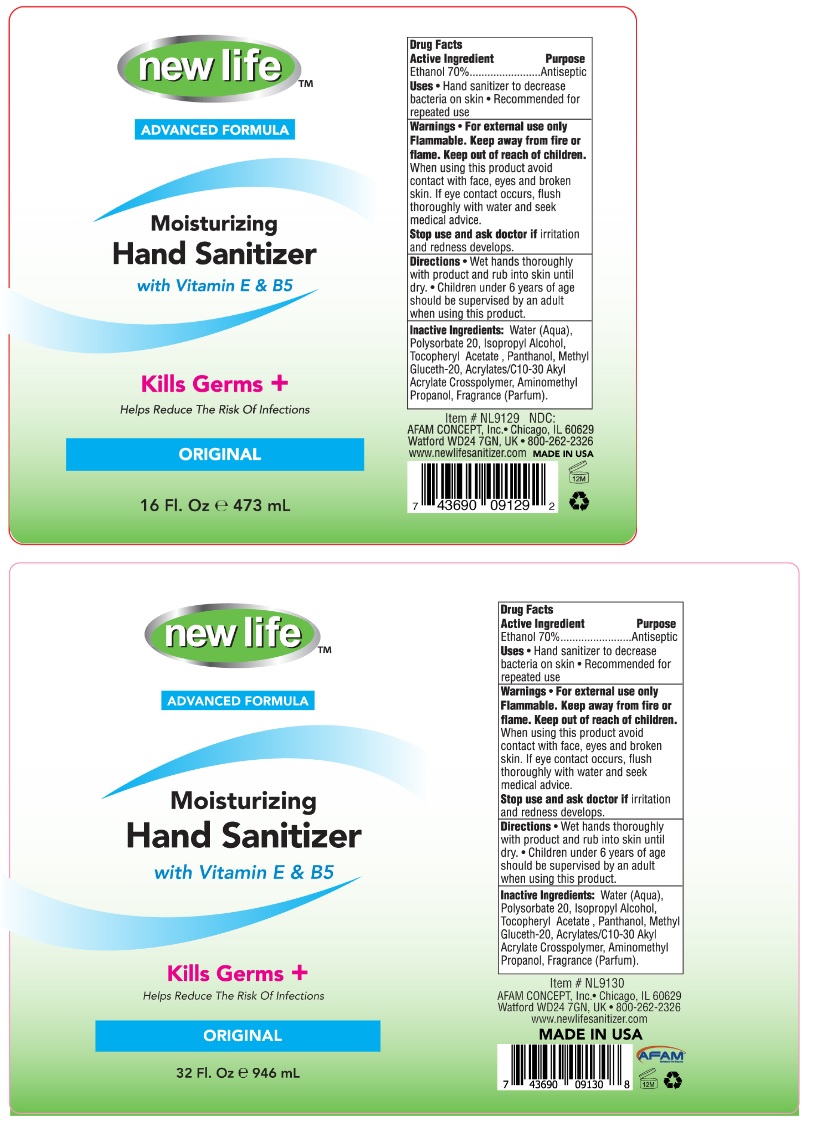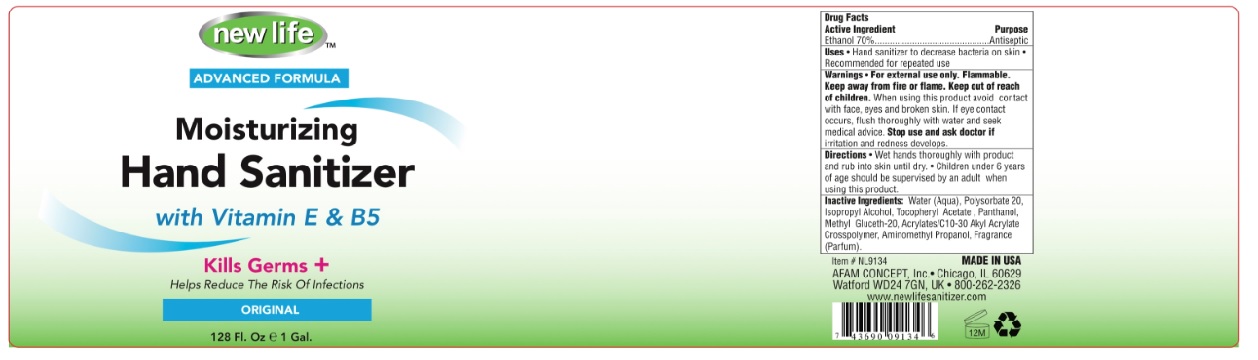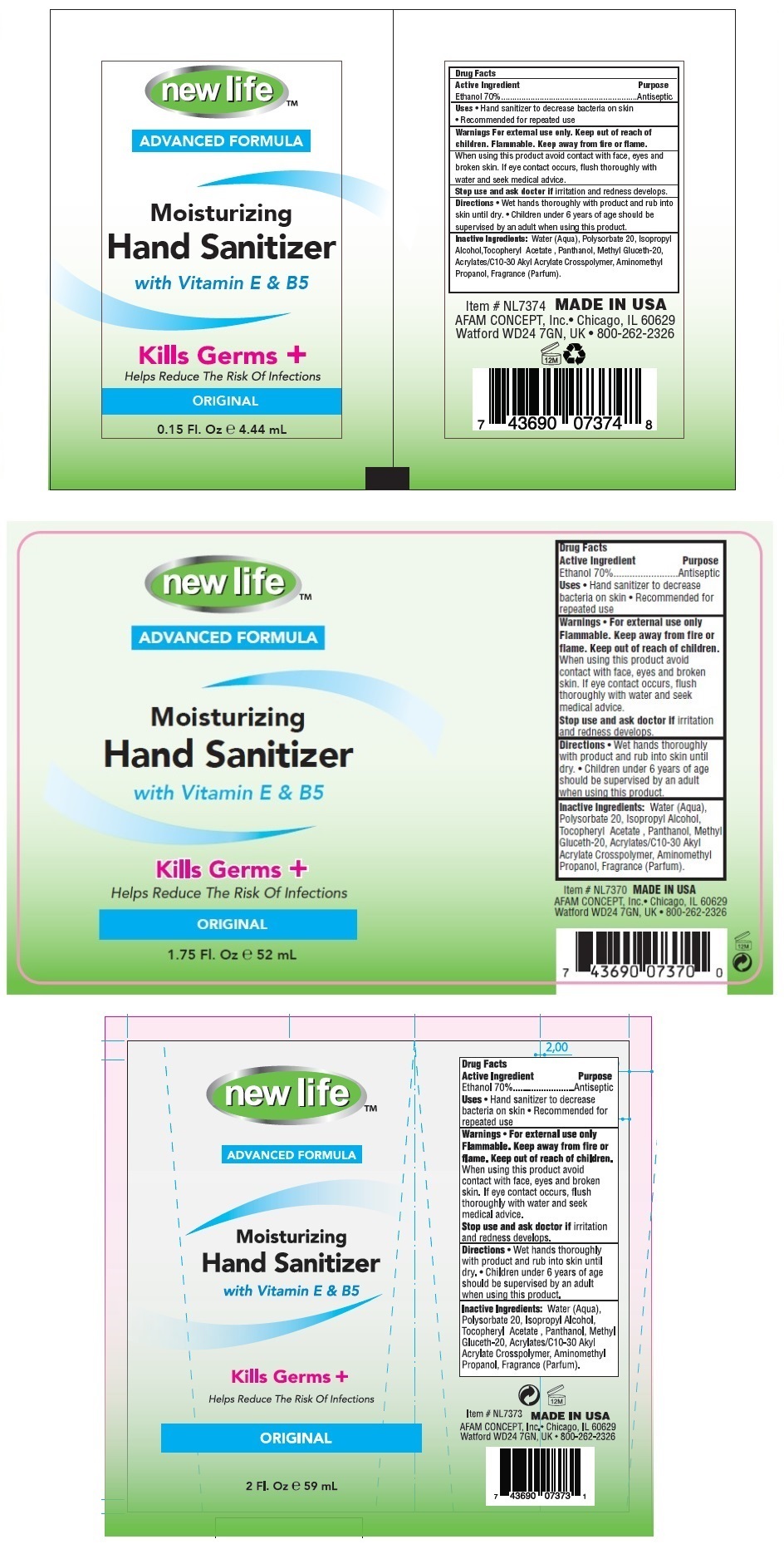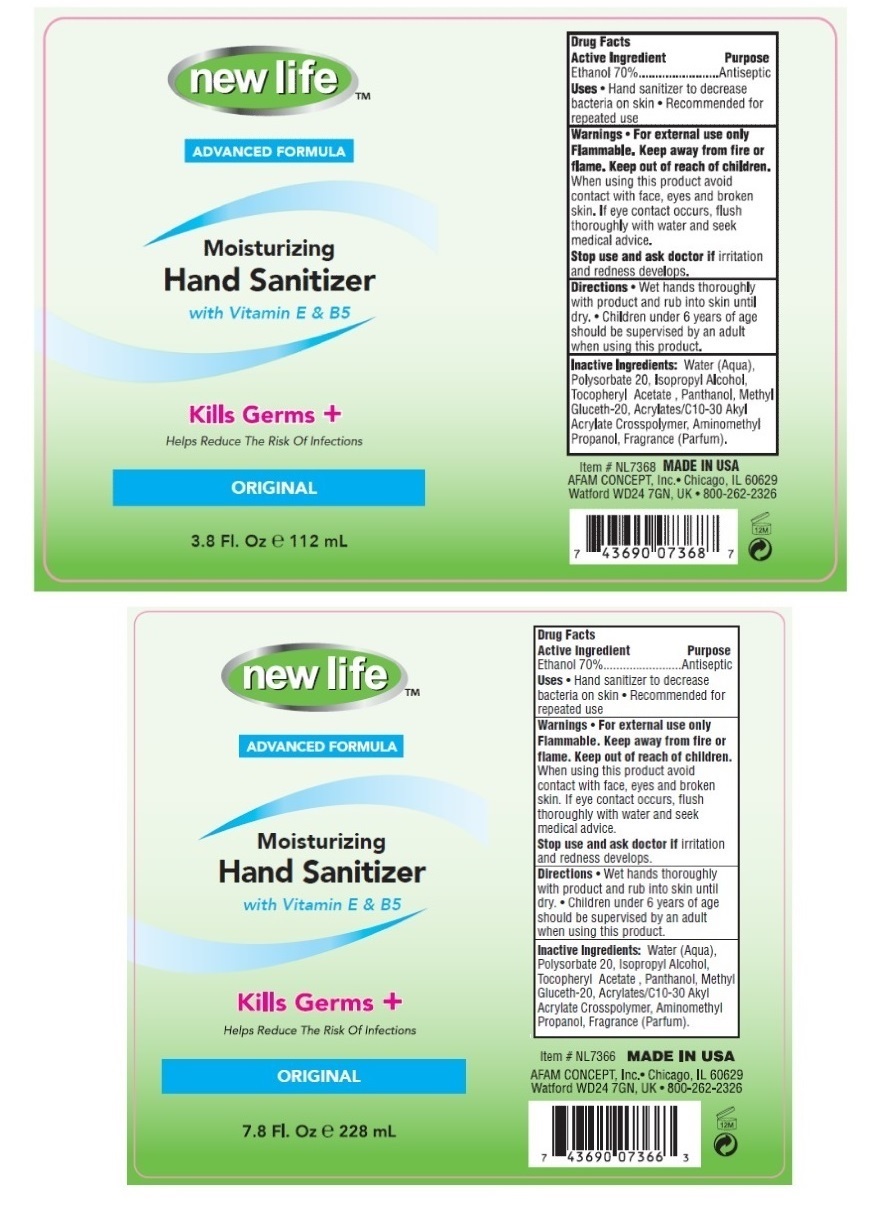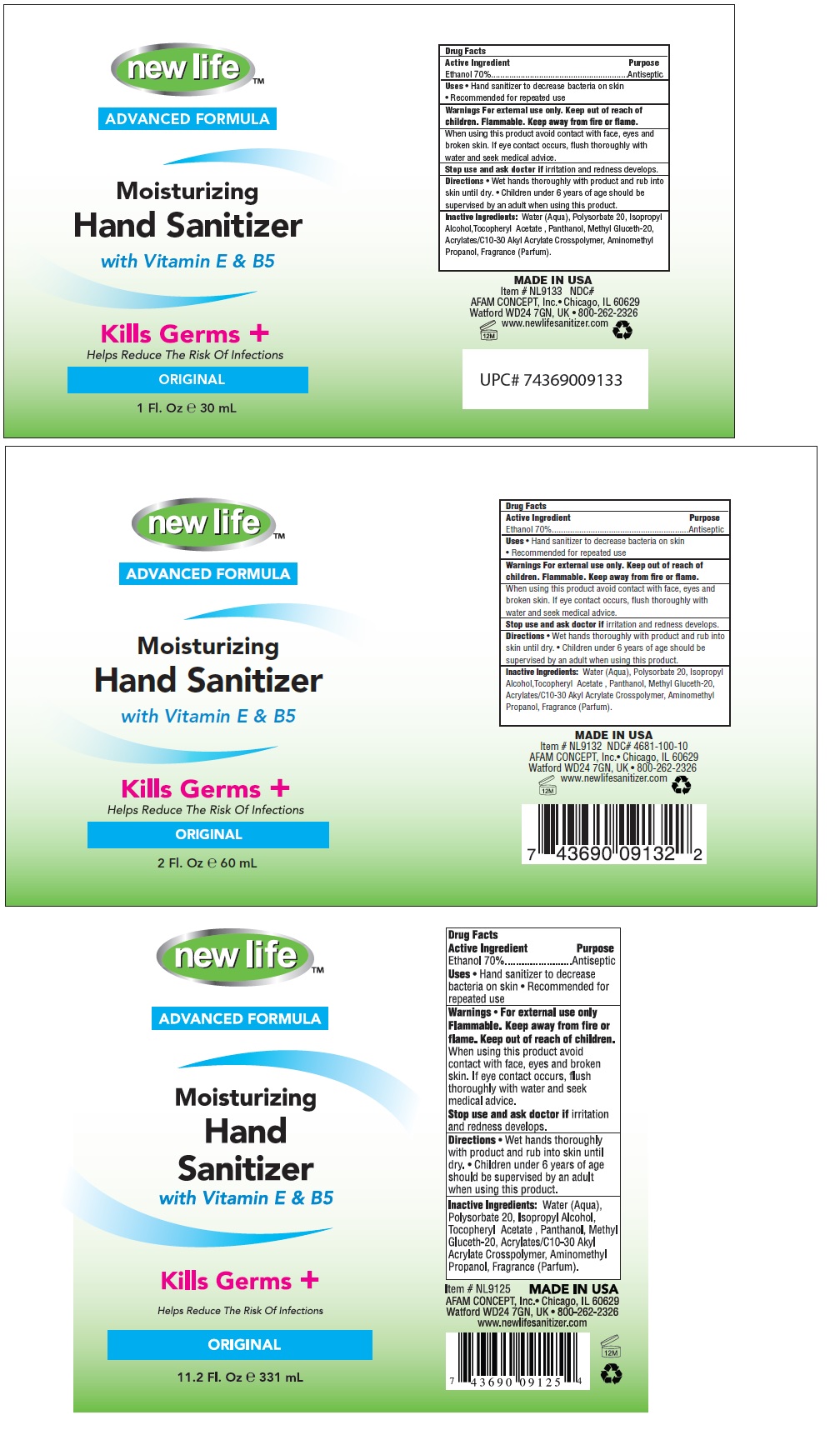 DRUG LABEL: new life Moisturizing Hand Sanitizer
NDC: 49681-100 | Form: GEL
Manufacturer: New Life Products, Inc.
Category: otc | Type: HUMAN OTC DRUG LABEL
Date: 20230202

ACTIVE INGREDIENTS: ALCOHOL 70 mL/100 mL
INACTIVE INGREDIENTS: WATER; POLYSORBATE 20; ISOPROPYL ALCOHOL; .ALPHA.-TOCOPHEROL ACETATE; PANTHENOL; METHYL GLUCETH-20; CARBOMER INTERPOLYMER TYPE A (ALLYL SUCROSE CROSSLINKED); AMINOMETHYLPROPANOL

new life Moisturizing Hand Sanitizer

Active Ingredient

Ethanol 70%

Purpose

Antiseptic

INDICATIONS AND USAGE

Uses • Hand sanitizer to decrease bacteria on skin • Recommended for repeated use

Warnings • For external use only

Flammable. Keep away from fire or flame.

When using this product avoid contact with face, eyes and broken skin. If eye contact occurs, flush thoroughly with water and seek medical advice.

Stop use and ask doctor if irritation and redness develops.

Keep out of reach of children.

DOSAGE AND ADMINISTRATION

Directions • Wet hands thoroughly with product and rub into skin until dry. • Children under 6 years of age should be supervised by an adult when using this product.

INACTIVE INGREDIENT

Inactive Ingredients: Water (Aqua), Polysorbate 20, Isopropyl Alcohol, Tocopheryl Acetate, Panthenol, Methyl Gluceth-20, Acrylates/C10-30 Alkyl Acrylate Crosspolymer, Aminomethyl Propanol, Fragrance (Parfum).

new life™

ADVANCED FORMULA

Moisturizing Hand Sanitizer with Vitamin E & B5

Kills Germs +

Helps Reduce The Risk Of Infections

ORIGINAL

MADE IN USA

AFAM CONCEPT, Inc. • Chicago, IL 60629

Watford WD24 7GN, UK • 800-262-2326